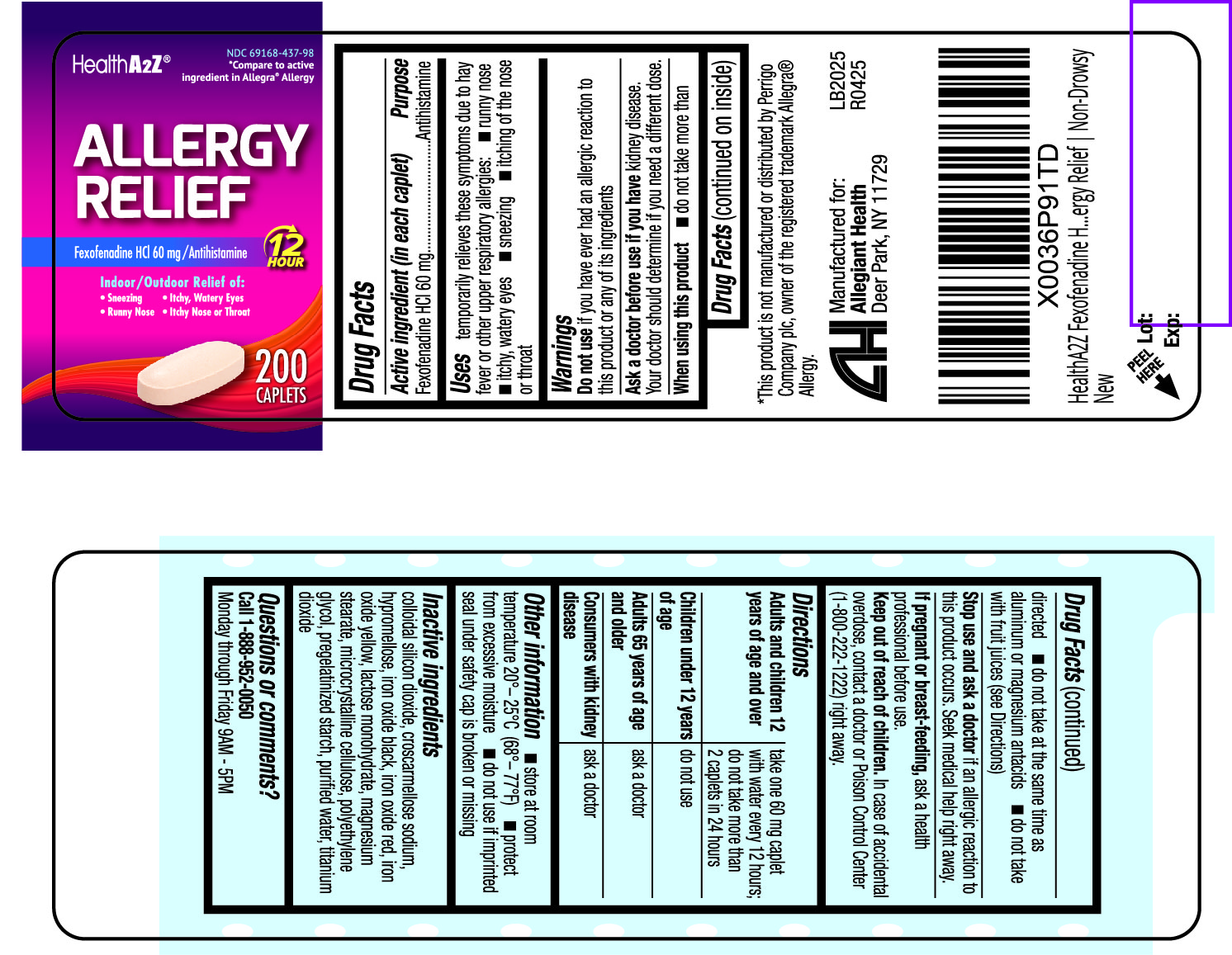 DRUG LABEL: Allergy Relief
NDC: 69168-437 | Form: TABLET, FILM COATED
Manufacturer: Allegiant Health
Category: otc | Type: HUMAN OTC DRUG LABEL
Date: 20220519

ACTIVE INGREDIENTS: FEXOFENADINE HYDROCHLORIDE 60 mg/1 1
INACTIVE INGREDIENTS: CROSCARMELLOSE SODIUM; FERROSOFERRIC OXIDE; FERRIC OXIDE RED; FERRIC OXIDE YELLOW; LACTOSE MONOHYDRATE; HYPROMELLOSE, UNSPECIFIED; MAGNESIUM STEARATE; MICROCRYSTALLINE CELLULOSE; POLYETHYLENE GLYCOL, UNSPECIFIED; SILICON DIOXIDE; STARCH, CORN; TITANIUM DIOXIDE

437 - Allergy Relief

Active ingredient(s)

Fexofenadine HCl 60mg

Purpose

Antihistamine

Use(s)

temporarily relieves these symptoms due to hay fever or other upper respiratory
allergies:

- runny nose
- itchy, watery eyes
- sneezing
- itching of the nose or throat

Warnings

Do not use

if you have ever had an allergic reaction to this product or any of its ingredients

Ask a doctor before use if

you have kidney disease. Your doctor should determine if you need a different dose.

When using this product

- do not take more than directed
- do not take at the same time as aluminum or magnesium antacids
- do not take with fruit juices (see Directions)

Stop use and ask a doctor if

an allergic reaction to this product occurs. Seek medical help right away.

Pregnancy/Breastfeeding

ask a health professional before use.

Keep out of reach of children

In case of accidental overdose, contact a doctor or Poison Control Center (1-800-222-1222) right away.

Directions

Adults and children 12 years of age and over: take one 60 mg caplet with water every 12 hours; do not take more than 2 caplets in 24 hours

Children under 12 years of age: do not use

Adults 65 years of age and older: ask a doctor

Consumers with kidney disease: ask a doctor

Other information

- store at room temperature 20°– 25°C (68°– 77°F)

- protect from excessive moisture

- do not use if imprinted seal under safety cap is broken or missing

Inactive ingredients

colloidal silicon dioxide, croscarmellose sodium, hypromellose, iron oxide black, iron oxide red, iron
oxide yellow, lactose monohydrate, magnesium stearate, microcrystalline cellulose, polyethylene
glycol, pregelatinized starch, purified water, titanium dioxide

Questions

Questions or comments?
Call 1-888-952-0050
Monday through Friday 9AM - 5PM

Principal Display Panel

Allergy Relief